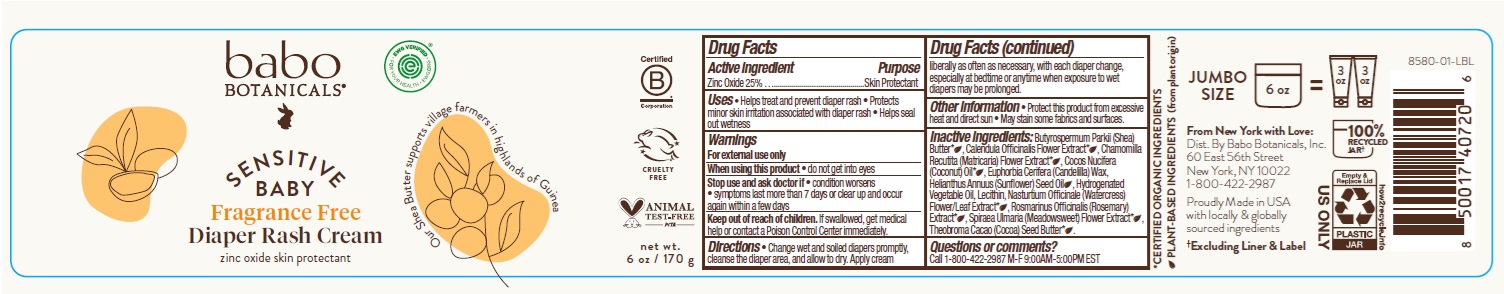 DRUG LABEL: Babo Botanicals Sensitive Baby Fragrance Free Diaper Rash
NDC: 79265-8580 | Form: CREAM
Manufacturer: Babo Botanicals, Inc.
Category: otc | Type: HUMAN OTC DRUG LABEL
Date: 20240514

ACTIVE INGREDIENTS: ZINC OXIDE 250 mg/1 g
INACTIVE INGREDIENTS: FILIPENDULA ULMARIA FLOWER; SHEA BUTTER; CHAMOMILE; NASTURTIUM OFFICINALE FLOWERING TOP; COCOA BUTTER; CALENDULA OFFICINALIS FLOWER; LECITHIN, SUNFLOWER; ROSEMARY; COCONUT OIL; SUNFLOWER OIL; CANDELILLA WAX

Babo Botanicals Sensitive Baby Fragrance Free Diaper Rash Cream

Active ingredient

Zinc Oxide 25%

Purpose

Skin Protectant

Uses

- Helps treat and prevent diaper rash
- Protects minor skin irritation associated with diaper rash
- Helps seal out wetness

Warnings

For external use only

When using this product

- do not get into eyes

Stop use and ask doctor if

- condition worsens
- symptoms last more than 7 days or clear up and occur again within a few days

Keep out of reach of children.

If swallowed, get medical help or contact a Poison Control Center immediately.

Directions

- Change wet and soiled diapers promptly, cleanse the diaper area, and allow to dry. Apply cream liberally as often as necessary, with each diaper change, especially at bedtime or anytime when exposure to wet diapers may be prolonged.

Other information

- Protect this product from excessive heat and direct sun
- May stain some fabrics and surfaces

Inactive ingredients

Butyrospermum Parkii (Shea) Butter*, Calendula Officinalis Flower Extract*, Chamomilla Recutita (Matricaria) Flower Extract*, Cocos Nucifera (Coconut) Oil*, Euphorbia Cerifera (Candelilla) Wax, Helianthus Annuus (Sunflower) Seed Oil, Hydrogenated Vegetable Oil, Lecithin, Nasturtium Officinale (Watercress) Flower/Leaf Extract*, Rosmarinus Officinalis (Rosemary) Extract*, Spiraea Ulmaria (Meadowsweet) Flower Extract*, Theobroma Cacao (Cocoa) Seed Butter*

*CERTIFIED ORGANIC INGREDIENTS

Questions or comments?

Call 1-800-422-2987 M-F 9:00AM-5:00PM EST